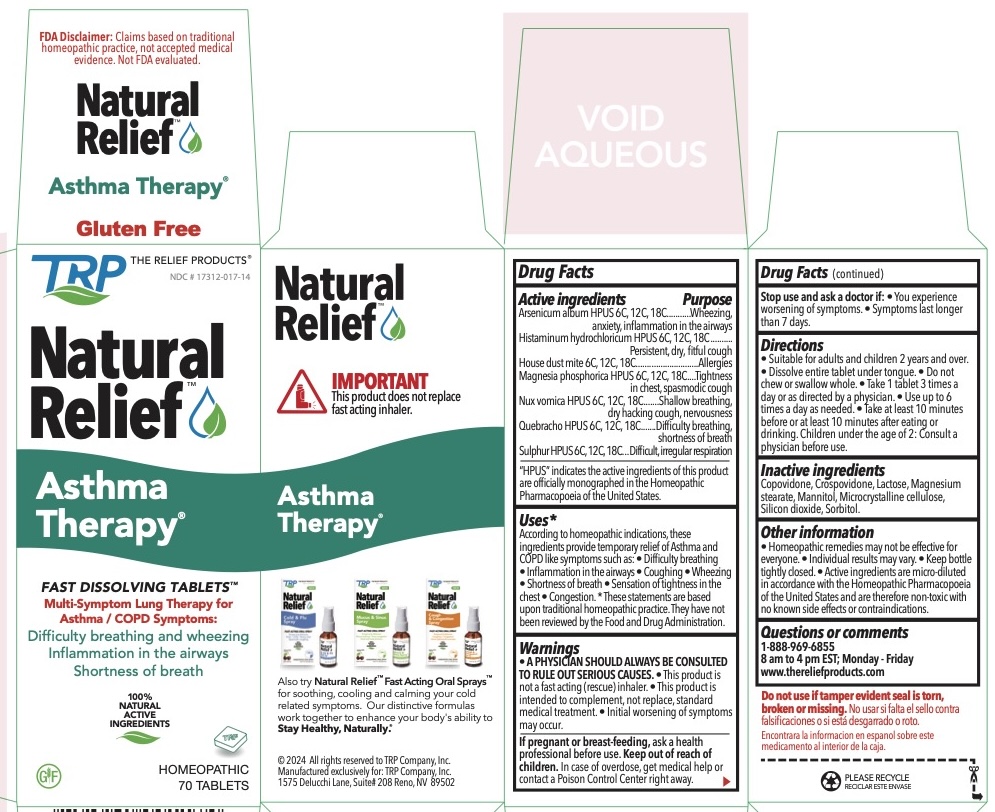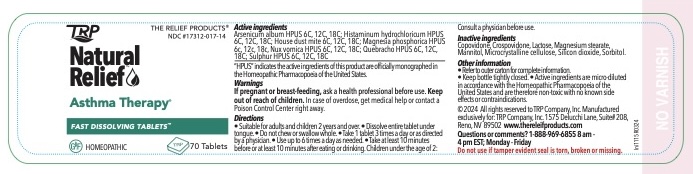 DRUG LABEL: Asthma Therapy
NDC: 17312-017 | Form: TABLET, ORALLY DISINTEGRATING
Manufacturer: TRP Company
Category: homeopathic | Type: HUMAN OTC DRUG LABEL
Date: 20251215

ACTIVE INGREDIENTS: STRYCHNOS NUX-VOMICA SEED 6 [hp_C]/1 1; ASPIDOSPERMA QUEBRACHO-BLANCO BARK 6 [hp_C]/1 1; SULFUR 6 [hp_C]/1 1; ARSENIC TRIOXIDE 6 [hp_C]/1 1; HISTAMINE DIHYDROCHLORIDE 6 [hp_C]/1 1; DERMATOPHAGOIDES PTERONYSSINUS 6 [hp_C]/1 1; MAGNESIUM PHOSPHATE, DIBASIC TRIHYDRATE 6 [hp_C]/1 1
INACTIVE INGREDIENTS: MANNITOL; SORBITOL; CROSPOVIDONE; CELLULOSE, MICROCRYSTALLINE; COPOVIDONE; SILICON DIOXIDE; LACTOSE; MAGNESIUM STEARATE

Asthma Therapy™ Homeopathic Fast Dissolving Tablets

Active Ingredients |  | Purpose
Arsenicum album HPUS | 6c/12c/18c | Wheezing, Anxiety, Inflammation in the airways
Histaminum hydrochloricum HPUS | 6c/12c/18c | Persistent, Dry, Fitful cough
House Dust Mite | 6c/12c/18c | Allergies
Magnesia Phosphorica HPUS | 6c/12c/18c | Tightness in chest, Spasmodic cough
Nux Vomica HPUS | 6c/12c/18c | Shallow breathing, Dry hacking cough, Nervousness
Quebracho HPUS | 6c/12c/18c | Difficulty breathing, Shortness of breath
Sulphur HPUS | 6c/12c/18c | Difficult, Irregular respiration

The letters HPUS indicate that the components of this product are officially monographed in the Homeopathic Pharmacopoeia of the United States.

Uses

According to homeopathic indications, these ingredients provide temporary relief of Asthma and COPD like symptoms such as: • Difficulty Breathing • Inflammation in the airways • Coughing • Wheezing • Shortness of breath • Sensation of tightness of the chest • Congestion after a diagnosis of Asthma or COPD by a physician.

Warnings

USE ONLY AFTER DIAGNOSIS BY A PHYSICIAN.

- This product is a not a fast acting (rescue) inhaler.
- This product is intended to complement, not replace, standard medical treatment.
- Initial worsening of symptoms may occur.
- A physician should always be consulted to rule out serious causes.
- In case of overdose, get medical help or contact a Poison Control Center right away.

Stop use and ask a doctor if:

- You experience worsening symptoms.
- If symptoms last longer than 7 days.

PREGNANCY OR BREAST FEEDING

If pregnant or breast-feeding, ask a health professional before use.

Directions

- Suitable for adults and children 12 years and above.
- Dissolve entire tablet under tongue.
- Do not chew or swallow whole.
- Take 1 tablet 3 times a day or as directed by a physician.
- Use up to 6 times a day as needed.
- Take at least 10 minutes before or at least 10 minutes after eating or drinking.
- Children under the age of 12: consult a physician before use.

Other information

- Active ingredients are micro-diluted in accordance with the Homeopathic Pharmacopoeia of the United States and are therefore non-toxic with no known side effects.
- Store in a cool dark location.

Inactive Ingredients

Advantol® 300, Lactose, Magnesium Stearate, Mannitol, Microcrystalline Cellulose.

QUESTIONS

For more information and to order related products call toll free: 888-969-6855 or trpcompany.com

Principal Display Panel

FDA Disclaimer: Claims based on traditional
homeopathic practice, not accepted medical
evidence. Not FDA evaluated.